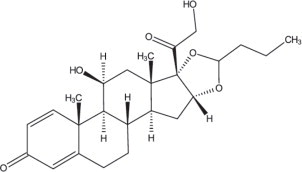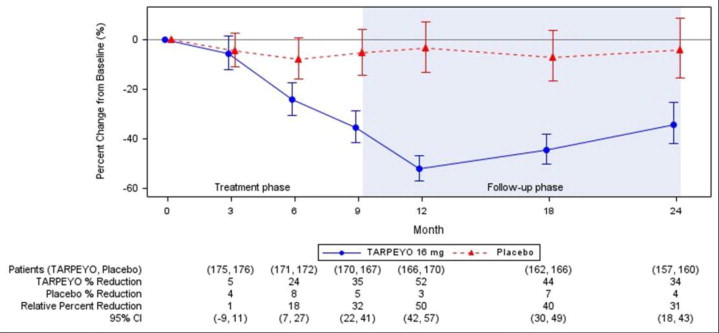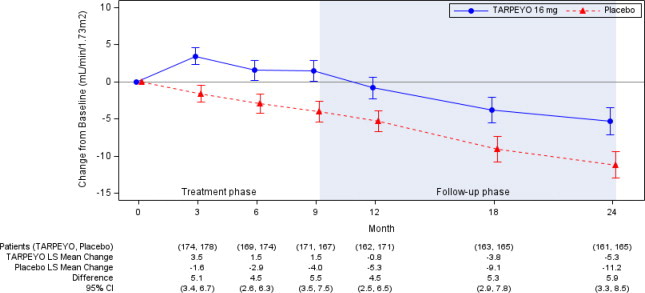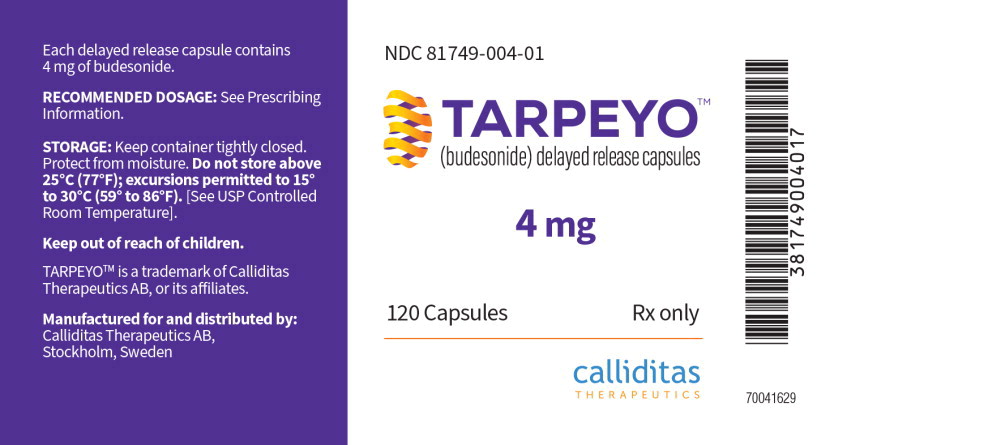 DRUG LABEL: Tarpeyo
NDC: 81749-004 | Form: CAPSULE, DELAYED RELEASE
Manufacturer: Calliditas Therapeutics AB
Category: prescription | Type: HUMAN PRESCRIPTION DRUG LABEL
Date: 20260121

ACTIVE INGREDIENTS: BUDESONIDE 4 mg/1 1
INACTIVE INGREDIENTS: SUCROSE; STARCH, CORN; HYPROMELLOSE 2910 (5 MPA.S); HYPROMELLOSE, UNSPECIFIED; HYPROMELLOSE 2910 (3 MPA.S); POLYETHYLENE GLYCOL 400; CITRIC ACID MONOHYDRATE; ETHYLCELLULOSE (10 MPA.S); MEDIUM-CHAIN TRIGLYCERIDES; OLEIC ACID; TITANIUM DIOXIDE; SHELLAC; PROPYLENE GLYCOL; FERROSOFERRIC OXIDE; METHACRYLIC ACID - METHYL METHACRYLATE COPOLYMER (1:2); METHACRYLIC ACID - METHYL METHACRYLATE COPOLYMER (1:1); TALC; DIBUTYL SEBACATE

HIGHLIGHTS OF PRESCRIBING INFORMATION

These highlights do not include all the information needed to use TARPEYO safely and effectively. See full prescribing information for TARPEYO.
TARPEYO (budesonide) delayed release capsules, for oral use
Initial U.S. Approval: 1997

1 INDICATIONS AND USAGE

TARPEYO is a corticosteroid indicated to reduce the loss of kidney function in adults with primary immunoglobulin A nephropathy (IgAN) who are at risk for disease progression. (1)

2 DOSAGE AND ADMINISTRATION

- The recommended dosage is 16 mg administered orally once daily, in the morning at least 1 hour before a meal. (2)
- Swallow whole. Do not open, crush or chew. (2)
  When discontinuing, reduce dosage to 8 mg once daily for the last two weeks. (2, 5.1)

3 DOSAGE FORMS AND STRENGTHS

Delayed release capsules: 4 mg (3)

4 CONTRAINDICATIONS

- Hypersensitivity to budesonide or any of the ingredients in TARPEYO. (4)

5 WARNINGS AND PRECAUTIONS

- Hypercorticism and Adrenal Axis Suppression:Follow general warnings concerning corticosteroids, patients with hepatic impairment may be at increased risk. Taper upon discontinuation. (2, 5.1, 8.6, 12.3)
- Immunosuppression and Increased Risk of Infection:Avoid use in patients with active or quiescent tuberculosis infection, untreated fungal, bacterial, systemic viral or parasitic infections, or ocular herpes simplex. May affect vaccine efficacy. (5.2)
- Other Corticosteroid Effects:Monitor patients with concomitant conditions where corticosteroids may have unwanted effects (e.g., hypertension, diabetes mellitus). (5.3)

6 ADVERSE REACTIONS

Most common adverse reactions (≥5%) are peripheral edema, hypertension, muscle spasms, acne, headache, upper respiratory tract infection, face edema, weight increased, dyspepsia, dermatitis, arthralgia, white blood cell count increased. (6.1)

To report SUSPECTED ADVERSE REACTIONS, contact Calliditas Therapeutics at 1-844-IGA-0011 or FDA at 1-800-FDA-1088 orwww.fda.gov/medwatch.

7 DRUG INTERACTIONS

Potent CYP3A4 Inhibitors (e.g. ketoconazole, grapefruit juice): Can increase systemic budesonide concentrations: avoid concomitant use. (7.1)

8 USE IN SPECIFIC POPULATIONS

Lactation: Routine monitoring of linear growth in infants is recommended with chronic use of budesonide in the nursing mother. (8.2).

FULL PRESCRIBING INFORMATION

1 INDICATIONS AND USAGE

TARPEYO is indicated to reduce the loss of kidney function in adults with primary immunoglobulin A nephropathy (IgAN) who are at risk for disease progression.

2 DOSAGE AND ADMINISTRATION

The recommended duration of therapy is 9 months, with a dosage of 16 mg administered orally once daily [see Clinical Studies (14.1)] . When discontinuing therapy, reduce the dosage to 8 mg once daily for the last 2 weeks of therapy [see Warnings and Precautions (5.1)] .

The delayed release capsules should be swallowed whole in the morning, at least 1 hour before a meal. Do not open, crush or chew.

If a dose is missed, take the prescribed dose at the next scheduled time. Do not double the next dose.

Safety and efficacy of treatment with subsequent courses of TARPEYO have not been established.

3 DOSAGE FORMS AND STRENGTHS

Delayed release capsule containing 4 mg budesonide. White coated opaque capsules printed with “CAL10 4MG” in black ink.

4 CONTRAINDICATIONS

TARPEYO is contraindicated in patients with hypersensitivity to budesonide or any of the ingredients of TARPEYO. Serious hypersensitivity reactions, including anaphylaxis have occurred with other budesonide formulations.

5 WARNINGS AND PRECAUTIONS

5.1 Hypercorticism and Adrenal Axis Suppression

When corticosteroids are used chronically, systemic effects such as hypercorticism and adrenal suppression may occur. Corticosteroids can reduce the response of the hypothalamus-pituitary-adrenal (HPA) axis to stress. In situations where patients are subject to surgery or other stress situations, supplementation with a systemic corticosteroid is recommended. When discontinuing therapy [see Dosing and Administration (2)] or switching between corticosteroids, monitor for signs of adrenal axis suppression.

Patients with moderate to severe hepatic impairment (Child-Pugh Class B and C respectively) could be at an increased risk of hypercorticism and adrenal axis suppression due to an increased systemic exposure of oral budesonide. Avoid use in patients with severe hepatic impairment (Child-Pugh Class C). Monitor for increased signs and/or symptoms of hypercorticism in patients with moderate hepatic impairment (Child-Pugh Class B) [see Use in Specific Populations (8.6), Clinical Pharmacology (12.3)] .

5.2 Immunosuppression and Increased Risk of Infection

Corticosteroids, including TARPEYO, suppress the immune system and increase the risk of infection with any pathogen, including viral, bacterial, fungal, protozoan, or helminthic pathogens. Corticosteroids can:

- Reduce resistance to new infections
- Exacerbate existing infections
- Increase the risk of disseminated infections
- Increase the risk of reactivation or exacerbation of latent infections
- Mask some signs of infection

Corticosteroid-associated infections can be mild but can be severe and at times fatal. The rate of infectious complications increases with increasing corticosteroid dosages.

Monitor for the development of infection and consider TARPEYO withdrawal as needed.

Tuberculosis

If TARPEYO is used to treat a condition in patients with latent tuberculosis or tuberculin reactivity, reactivation of tuberculosis may occur. In patients with latent tuberculosis or tuberculin reactivity TARPEYO should be discontinued.

Varicella Zoster and Measles Viral Infections

Varicella and measles can have a serious or even fatal course in non-immune patients taking corticosteroids, including TARPEYO. In corticosteroid-treated patients who have not had these diseases or are non-immune, particular care should be taken to avoid exposure to varicella and measles:

- If a TARPEYO-treated patient is exposed to varicella, prophylaxis with varicella zoster immune globulin may be indicated. If varicella develops, treatment with antiviral agents may be considered.
- If a TARPEYO-treated patient is exposed to measles, prophylaxis with immunoglobulin may be indicated.

Hepatitis B Virus Reactivation

Hepatitis B virus reactivation can occur in patients who are hepatitis B carriers treated with immunosuppressive dosages of corticosteroids, including TARPEYO. Reactivation can also occur infrequently in corticosteroid-treated patients who appear to have resolved hepatitis B infection.

Screen patients for hepatitis B infection before initiating immunosuppressive treatment with TARPEYO. For patients who show evidence of hepatitis B infection, recommend consultation with physicians with expertise in managing hepatitis B regarding monitoring and consideration for hepatitis B antiviral therapy.

Fungal Infections

Corticosteroids, including TARPEYO, may exacerbate systemic fungal infections; therefore, avoid TARPEYO use in the presence of such infections.

Amebiasis

Corticosteroids, including TARPEYO, may activate latent amebiasis. Therefore, it is recommended that latent amebiasis or active amebiasis be ruled out before initiating TARPEYO in patients who have spent time in the tropics or patients with unexplained diarrhea.

Strongyloides Infestation

Corticosteroids, including TARPEYO, should be discontinued in patients with known or suspected Strongyloides (threadworm) infestation. In such patients, corticosteroid-induced immunosuppression may lead to Strongyloides hyperinfection and dissemination with widespread larval migration, often accompanied by severe enterocolitis and potentially fatal gram-negative septicemia.

Cerebral Malaria

Avoid corticosteroids, including TARPEYO, in patients with cerebral malaria.

Ocular Herpes Simplex Virus Infection

Corticosteroids, including TARPEYO, may exacerbate ocular herpes simplex virus infections; therefore, avoid TARPEYO use in the presence of such infections.

Kaposi's Sarcoma

Kaposi's sarcoma has been reported to occur in patients receiving corticosteroid therapy, most often for chronic conditions. Discontinuation of corticosteroids may result in clinical improvement of Kaposi's sarcoma.

Immunizations

Corticosteroid therapy, including TARPEYO, may decrease the immune response to some vaccines.

5.3 Other Corticosteroid Effects

TARPEYO is a systemically available corticosteroid and is expected to cause related adverse reactions. Monitor patients with hypertension, prediabetes, diabetes mellitus, osteoporosis, peptic ulcer, glaucoma or cataracts, or with a family history of diabetes or glaucoma, or with any other condition where corticosteroids may have unwanted effects.

6 ADVERSE REACTIONS

The following clinically significant adverse reactions are described elsewhere in the labeling:

- Hypercorticism and adrenal axis suppression [see Warnings and Precautions (5.1)]
- Risks of immunosuppression [see Warnings and Precautions (5.2)]
- Other corticosteroid effects [see Warnings and Precautions (5.3)]

6.1 Clinical Trials Experience

Because clinical trials are conducted under widely varying conditions, adverse reaction rates observed in the clinical trials of a drug cannot be directly compared to rates in the clinical trials of another drug and may not reflect the rates observed in practice.

The safety of TARPEYO was evaluated in 389 patients in the randomized, double-blind, placebo-controlled study, NefIgArd (NCT: 03643965, Phase 3 clinical study in adults with primary IgAN). The data below reflect TARPEYO exposure in 195 patients with a median duration of 41 weeks, compared with comparable exposure to placebo in 194 patients.

The most common adverse reactions, reported in greater than or equal to 5% of TARPEYO-treated patients and greater than or equal to 2% higher than placebo, in the 9-month treatment period are listed in Table 1.

Most adverse reactions that occurred at a greater incidence for TARPEYO compared to placebo were consistent with hypercortisolism and reversible, resolving within 3 months after discontinuation.

Table 1: Reported adverse reactions occurring in greater than or equal to 5% of TARPEYO treated patients, and greater than or equal to 2% higher than Placebo
Adverse Reaction | TARPEYO 16 mg (N=195) | Placebo (N=194)
 | n (%) | n (%)
Peripheral edema | 33 (17) | 10 (5)
Hypertension | 23 (12) | 6 (3)
Muscle spasms | 23 (12) | 8 (4)
Acne | 22 (11) | 2 (1)
Headache | 19 (10) | 14 (7)
Upper respiratory tract infection | 16 (8) | 12 (6)
Face edema | 15 (8) | 1 (0.5)
Weight increased | 13 (7) | 6 (3)
Dyspepsia | 13 (7) | 4 (2)
Dermatitis | 12 (6) | 2 (1)
Arthralgia | 12 (6) | 4 (2)
White blood cell count increased | 11 (6) | 1 (0.5)

7 DRUG INTERACTIONS

7.1 Interaction with CYP3A4 Inhibitors

Budesonide is a substrate for CYP3A4. Avoid use with potent CYP3A4 inhibitors; e.g. ketoconazole, itraconazole, ritonavir, indinavir, saquinavir, erythromycin, and cyclosporine [see Clinical Pharmacology (12.3)] .

Avoid ingestion of grapefruit juice with TARPEYO. Intake of grapefruit juice, which inhibits CYP3A4 activity, can increase the systemic exposure to budesonide [see Clinical Pharmacology (12.3)] .

8 USE IN SPECIFIC POPULATIONS

8.1 Pregnancy

Risk Summary

The available data from published case series, epidemiological studies and reviews with oral budesonide use in pregnant women have not identified a drug-associated risk of major birth defects, miscarriage or other adverse maternal or fetal outcomes. There are risks to the mother and fetus associated with IgA Nephropathy. Infants exposed to in utero corticosteroids, including budesonide, are at risk for hypoadrenalism (see Clinical Considerations) . In animal reproduction studies with pregnant rats and rabbits, administration of subcutaneous budesonide during organogenesis at doses approximately 0.3 times or 0.03 times, respectively, the maximum recommended human dose (MRHD), resulted in increased fetal loss, decreased pup weights, and skeletal abnormalities. Maternal toxicity was observed in both rats and rabbits at these dose levels (see Data) .

The estimated background risk of major birth defects and miscarriage of the indicated population is unknown. All pregnancies have a background risk of birth defects, loss, or other adverse outcomes. In the U.S. general population, the estimated background risk of major birth defects and miscarriage in clinically recognized pregnancies is 2% to 4% and 15% to 20%, respectively.

Clinical Considerations

Disease-Associated Maternal and/or Embryo/Fetal Risk

IgA nephropathy in pregnancy is associated with adverse maternal outcomes, including increased rates of cesarean section, pregnancy-induced hypertension, pre-eclampsia and preterm delivery, and adverse fetal/neonatal outcomes, including stillbirth and low birth weight.

Fetal/Neonatal Adverse Reactions

Hypoadrenalism may occur in infants born to mothers receiving corticosteroids during pregnancy. Infants should be carefully observed for signs of hypoadrenalism, such as poor feeding, irritability, weakness, and vomiting, and managed accordingly [see Warnings and Precautions (5.1)].

Data

Animal Data

Budesonide was teratogenic and embryo-lethal in rabbits and rats.

In an embryo-fetal development study in pregnant rats dosed subcutaneously with budesonide during the period of organogenesis on gestation days 6 to 15 there were effects on fetal development and survival at subcutaneous doses up to approximately 500 mcg/kg in rats (approximately 0.3 times the maximum recommended human dose (MRHD) on a body surface area basis).

In an embryo-fetal development study in pregnant rabbits dosed during the period of organogenesis on gestation days 6 to 18, there was an increase in maternal abortion, and effects on fetal development and reduction in litter weights at subcutaneous doses from approximately 25 mcg/kg (approximately 0.03 times the MRHD on a body surface area basis).

Maternal toxicity, including reduction in body weight gain, was observed at subcutaneous doses of 5 mcg/kg in rabbits (approximately 0.006 times the maximum recommended human dose on a body surface area basis) and 500 mcg/kg in rats (approximately 0.3 times the maximum recommended human dose on a body surface area basis).

In a peri- and post-natal development study, subcutaneous treatment of pregnant rats with budesonide during the period from Day 15 post coitum to Day 21 post partum, budesonide had no effects on delivery, but did have an effect on growth and development of offspring. In addition, offspring survival was reduced and surviving offspring had decreased mean body weights at birth and during lactation at exposures ≥ 0.012 times the MRHD (on a mg/m^2basis at maternal subcutaneous doses of 20 mcg/kg/day and higher). These findings occurred in the presence of maternal toxicity.

8.2 Lactation

Risk Summary

Breastfeeding is not expected to result in significant exposure of the infant to TARPEYO. Lactation studies have not been conducted with oral budesonide, including TARPEYO, and no information is available on the effects of the drug on the breastfed infant or the effects of the drug on milk production. One published study reports that budesonide is present in human milk following maternal inhalation of budesonide (see Data). Routine monitoring of linear growth in infants is recommended with chronic use of budesonide in the nursing mother. The developmental and health benefits of breastfeeding should be considered along with the mother's clinical need for TARPEYO and any potential adverse effects on the breastfed infant from TARPEYO, or from the underlying maternal condition.

Data

One published study reports that budesonide is present in human milk following maternal inhalation of budesonide, which resulted in infant doses approximately 0.3% to 1% of the maternal weight-adjusted dosage and a milk to plasma ratio was approximately 0.5. Budesonide was not detected in plasma, and no adverse events were noted in the breastfed infants following maternal use of inhaled budesonide.

Assuming a daily average milk intake of about 150 mL/kg/day and a milk to plasma ratio of 0.5, the estimated oral dose of budesonide for a 5 kg infant is expected to be less than 2 mcg/day for a maternal dose of 16 mg TARPEYO. Assuming 100% bio-availability in the infant this is about 0.1% of the maternal dose and about 3% of the highest inhaled dose used clinically for asthma in infants.

8.4 Pediatric Use

The safety and efficacy of TARPEYO in pediatric patients have not been established.

8.5 Geriatric Use

Clinical studies of TARPEYO did not include sufficient numbers of subjects aged 65 and over to determine whether they respond differently from younger subjects. Other reported clinical experience has not identified differences in responses between the elderly and younger patients. In general, dose selection for an elderly patient should be cautious, reflecting the greater frequency of decreased hepatic, renal, or cardiac function, and of concomitant disease or other drug therapy.

8.6 Hepatic Impairment

Patients with moderate to severe hepatic impairment (Child-Pugh Class B and C, respectively) could be at an increased risk of hypercorticism and adrenal axis suppression due to an increased systemic exposure to budesonide [see Warnings and Precautions (5.1) and Clinical Pharmacology (12.3)] . Avoid use in patients with severe hepatic impairments (Child-Pugh Class C). Monitor for increased signs and/or symptoms of hypercorticism in patients with moderate hepatic impairment (Child-Pugh Class B).

10 OVERDOSAGE

Reports of acute toxicity and/or death following overdosage of corticoids are rare.

In the event of acute overdosage, no specific antidote is available. Treatment consists of supportive and symptomatic therapy.

11 DESCRIPTION

TARPEYO (budesonide) delayed release capsules, for oral administration, contain budesonide, a synthetic corticosteroid, as the active ingredient. Budesonide is designated chemically as 16α, 17α-[(1RS)-Butylidenebis(oxy)]-11β, 21-dihydroxypregna-1,4-diene-3,20-dione.

Budesonide is provided as a mixture of two epimers (22R and 22S). The empirical formula of budesonide is C25H34O6and its molecular weight is 430.5. Its structural formula is:

Budesonide is a white to off-white, tasteless, odorless powder that is practically insoluble in water, sparingly soluble in alcohol, and freely soluble in chloroform.

The beads in each capsule contain the following inactive ingredients: sugar spheres (sucrose and starch), hypromellose, polyethylene glycol, citric acid monohydrate, ethyl cellulose, medium chain triglycerides and oleic acid. The capsule shells contain hypromellose and titanium oxide (E171); and the printing ink on the capsules contain shellac, propylene glycol and black iron oxide (E172). The enteric coating on the capsules contain: methacrylic acid and methacrylate copolymer, talc and dibutyl sebacate.

12 CLINICAL PHARMACOLOGY

12.1 Mechanism of Action

Budesonide is a corticosteroid with potent glucocorticoid activity and weak mineralocorticoid activity that undergoes substantial first pass metabolism. Mucosal B-cells present in the ileum, including the Peyer's patches, express glucocorticoid receptors and are responsible for the production of galactose-deficient IgA1 antibodies (Gd-Ag1) causing IgA nephropathy. Through their anti-inflammatory and immunosuppressive effects at the glucocorticoid receptor, corticosteroids can modulate B-cell numbers and activity. It has not been established to what extent TARPEYO's efficacy is mediated via local effects in the ileum vs systemic effects.

12.2 Pharmacodynamics

Treatment with corticosteroids, including TARPEYO, is associated with a suppression of endogenous cortisol concentrations and an impairment of the hypothalamus-pituitary-adrenal (HPA) axis function.

12.3 Pharmacokinetics

Absorption

Following single oral administration of TARPEYO 16 mg to healthy subjects, the average geometric mean Cmax(CV%) was 4.4 ng/mL (58.3), and AUC0-24was 24.1 h*ng/mL (49.7). Median Tlag(min, max) was 3.1 h (0, 6) while median Tmax(min, max) was 5.1 h (4.5, 10).

Food Effect

There was no clinically relevant food effect observed on the overall systemic exposure of budesonide when either a moderate or high fat meal was consumed 1 hour after administration of TARPEYO.

Distribution

Approximately 85 to 90% of budesonide binds to plasma proteins in blood over the concentration range of 0.43 to 99 ng/mL. The volume of distribution at steady state reported in the literature is 3 to 4 L/kg.

Metabolism

Budesonide is metabolized by the liver (and to lesser extent the gut), primarily by oxidative pathways via CYP3A4 to two main metabolites, 16α-hydroxyprednisolone and 6β-hydroxybudesonide, which have less than 1% of the corticosteroid activity of budesonide.

Elimination

Budesonide had a high plasma clearance, 0.9 to 1.8 L/min in healthy adults, which is close to the estimated liver blood flow, and, accordingly, suggests that budesonide is a high hepatic clearance drug.

Following single oral administration of TARPEYO 16 mg to healthy subjects, the elimination half-life (t½) for TARPEYO ranged from 5.0 to 6.8 hours.

Excretion

Budesonide was excreted in urine and feces in the form of metabolites. After oral as well as intravenous administration of micronized [^3H]-budesonide, approximately 60% of the recovered radioactivity was found in urine. The major metabolites, including 16α-hydroxyprednisolone and 6β-hydroxybudesonide, are mainly renally excreted, intact or in conjugated forms. No unchanged budesonide was detected in urine.

Specific Populations

Age, race, and body weight

The effect of age, race, and body weight on the pharmacokinetics of TARPEYO has not been established.

Sex

Of the 143 healthy volunteers included in the Phase 1 studies, 29% were female. Pharmacokinetics of budesonide was similar between males and females.

Hepatic Impairment

Subjects with moderate hepatic impairment (Child-Pugh class B) had 3.5 times the budesonide AUC compared with healthy volunteers while subjects with mild hepatic impairment (Child-Pugh class A) had approximately 1.4 times the budesonide AUC compared with healthy volunteers.

Patients with severe hepatic impairment (Child-Pugh Class C) have not been studied.

Renal Impairment

Intact budesonide is not excreted renally. The main metabolites of budesonide, which have negligible corticosteroid activity, are largely (60%) excreted in urine.

Drug Interaction Studies

Budesonide is metabolized via CYP3A4. Potent inhibitors of CYP3A4 can increase plasma levels of budesonide.

Thus, clinically relevant drug interactions with potent CYP3A4 inhibitors, such as ketoconazole, itraconazole, ritonavir, indinavir, saquinavir, erythromycin, cyclosporine, and grapefruit juice, are to be expected. Conversely, induction of CYP3A4 potentially could result in the lowering of budesonide plasma concentrations.

Effects of Other Drugs on Budesonide

Ketoconazole

In an open, non-randomized, cross-over study, 6 healthy subjects were given budesonide 10 mg as a single dose, either alone or concomitantly with the last ketoconazole dose of 3 days treatment with ketoconazole 100 mg twice daily. Co-administration of ketoconazole resulted in 8-fold the AUC of budesonide, compared to budesonide alone.

In an open, randomized, cross-over study 8 healthy subjects were given Entocort EC 3 mg as a single dose, either alone or concomitantly with the last ketoconazole dose of 4 days treatment with ketoconazole 200 mg once daily. Co-administration of ketoconazole resulted in 6.5-fold the AUC of budesonide, compared to budesonide alone.

Grapefruit Juice

In an open, randomized, cross-over study, 8 healthy subjects were given Entocort EC 3 mg, either alone, or concomitantly with 600 mL concentrated grapefruit juice (which inhibits CYP3A4 activity predominantly in the intestinal mucosa), on the last of 4 daily administrations. Concomitant administration of grapefruit juice resulted in doubling the bioavailability of budesonide compared to budesonide alone.

Proton Pump Inhibitors

The pharmacokinetics of TARPEYO have not been evaluated in combination with proton pump inhibitors (PPIs). Since the disintegration of TARPEYO is pH dependent, the release properties and uptake of budesonide may be altered when TARPEYO is taken after treatment with PPIs. In a study assessing intragastric and intraduodenal pH in healthy volunteers after repeated dosing with the PPI omeprazole 40 mg once daily, intragastric and intraduodenal pH did not exceed that required for disintegration of TARPEYO. Beyond the duodenum, PPIs such as omeprazole are unlikely to affect pH.

Oral Contraceptives (CYP3A4 Substrates)

In a parallel study, the pharmacokinetics of budesonide were not significantly different between healthy female subjects who received oral contraceptives containing desogestrel 0.15 mg and ethinyl estradiol 30 μg and healthy female subjects who did not receive oral contraceptives. Budesonide 4.5 mg once daily for one week did not affect the plasma concentrations of ethinyl estradiol, a CYP3A4 substrate. The effect of budesonide 16 mg once daily on the plasma concentrations of desogestrel and ethinyl estradiol was not studied.

13 NONCLINICAL TOXICOLOGY

13.1 Carcinogenesis, Mutagenesis, Impairment of Fertility

Carcinogenicity studies with budesonide were conducted in rats and mice. In a two-year study in Sprague-Dawley rats, budesonide caused a statistically significant increase in the incidence of gliomas in male rats at an oral dose of 50 mcg/kg (approximately 0.03 times the maximum recommended human dose (MRHD) on a body surface area basis). In addition, there were increased incidences of primary hepatocellular tumors in male rats at 25 mcg/kg (approximately 0.015 times the MRHD on a body surface area basis) and above. No tumorigenicity was seen in female rats at oral doses up to 50 mcg/kg (approximately 0.03 times the MRHD on a body surface area basis). In an additional two-year study in male Sprague-Dawley rats, budesonide caused no gliomas at an oral dose of 50 mcg/kg (approximately 0.03 times the MRHD on a body surface area basis). However, it caused a statistically significant increase in the incidence of hepatocellular tumors at an oral dose of 50 mcg/kg (approximately 0.03 times the MRHD of a body surface area basis). The concurrent reference corticosteroids (prednisolone and triamcinolone acetonide) showed similar findings. In a 91-week study in mice, budesonide caused no treatment-related carcinogenicity at oral doses up to 200 mcg/kg (approximately 0.06 times the MRHD on a body surface area basis).

Budesonide was not genotoxic in the Ames test, the mouse lymphoma cell forward gene mutation (TK+/-) test, the human lymphocyte chromosome aberration test, the Drosophila melanogaster sex-linked recessive lethal test, the rat hepatocyte UDS test and the mouse micronucleus test.

In rats, budesonide had no effect on fertility at subcutaneous doses up to 80 mcg/kg (approximately 0.05 times the MRHD on a body surface area basis). However, it caused a decrease in prenatal viability and viability in pups at birth and during lactation, along with a decrease in maternal food consumption and body weight gain, at subcutaneous doses of 20 mcg/kg (approximately 0.012 times the MRHD on a body surface area basis) and above. No such effects were noted at 5 mcg/kg (approximately 0.003 times the MRHD on a body surface area basis).

14 CLINICAL STUDIES

14.1 Treatment of IgAN

TARPEYO was shown to reduce the loss of kidney function in adults with primary IgAN at risk of disease progression in the NefIgArd trial. While the effect on kidney function that was seen during the 9-month treatment period persisted following completion of treatment, TARPEYO did not change the long-term rate of decline in kidney function.

NefIgArd Study: A Phase 3, Double-Blind Placebo-Controlled, Randomized Trial in Adults with Primary IgAN

The effect of TARPEYO on proteinuria and kidney function (estimated glomerular filtration rate, eGFR) was assessed in a randomized, double-blind, phase 3, 2-part, multicenter study (NefIgArd, NCT: 03643965) in adults with biopsy-proven IgAN, eGFR ≥35 mL/min/1.73 m^2, and proteinuria (defined as either ≥1 g/day or urine protein to creatinine ratio (UPCR) ≥0.8 g/g) who were on a stable dose of maximally-tolerated RAS inhibitor therapy. Patients with other glomerulopathies, nephrotic syndrome, or those who had been treated with systemic immunosuppressive medications were excluded. Patients were randomized 1:1 to either TARPEYO 16 mg once daily or placebo and treated for nine months followed by a 2-week taper of either TARPEYO 8 mg once daily or placebo. Patients were then followed off-treatment for 15 months. The primary endpoint for Part A of the study (interim analysis) was the ratio of UPCR (based on 24-hour urine collections) at 9 months compared to baseline based on the first 199 randomized patients who completed the Month 9 visit. The primary endpoint for Part B of the study (final analysis) was a time-weighted average of the log ratio of eGFR at each time point over 2 years relative to baseline.

Of the 364 randomized patients evaluated for efficacy, 66% were male, 76% were Caucasian, 23% were Asian, and 20% were from North America. The median age was 43 years (range 20 to 73 years). At baseline, the mean eGFR was approximately 58 mL/min/1.73 m^2, with 60% of patients having an eGFR <60 mL/min/1.73 m^2. The mean baseline UPCR was 1.5 g/g and 21% of patients had proteinuria >3.5 g/24 hours. Approximately 70% of patients had a history of hypertension and 7% had a history of type 2 diabetes mellitus. At baseline, 98% were treated with an angiotensin-converting enzyme (ACE) inhibitor or angiotensin receptor blocker (ARB) and <1% of patients were on a sodium-glucose cotransporter 2 (SGLT2) inhibitor. At study entry, the median systolic/diastolic blood pressure was 125/79 mmHg.

The trial met the prespecified Part A primary endpoint based on an interim analysis of 199 randomized patients who had completed the Month 9 visit. The interim analysis showed a 31% reduction in UPCR in patients treated with TARPEYO 16 mg once daily compared to placebo (95% CI: 16% to 42% reduction; p=0.0001). In the final analysis of 364 patients, the percentage change in UPCR observed at 9 months was consistent with the results in the subset of 199 patients included in the interim analysis. The final analysis of the percentage change in UPCR during the treatment and follow-up phase is shown in Figure 1.

Figure 1: LS Mean (95% CI) Percentage Change from Baseline in UPCR (g/g) in NefIgArd Study (Full Analysis Set)

Estimated mean percentage change from baseline in UPCR with 95% confidence intervals estimated from a mixed model repeated measures analysis of log-transformed post-baseline to baseline ratios at 3, 6, 9, 12, 18, and 24 months. Analysis included all UPCR data regardless of use of prohibited medication at any point during the study.

Values reported under the figure are converted to percent reduction from baseline. Relative percent reductions comparing TARPEYO and placebo are estimated from the regression model.

Abbreviations: UPCR, urine protein to creatinine ratio; CI, confidence interval; LS, least squares.

In the final analysis of 364 patients, the trial met the prespecified Part B primary endpoint (p<0.0001). The mean change from baseline in eGFR and respective 95% CI for each arm at each scheduled visit during the treatment and follow-up phase is shown in Figure 2. The favorable effect of TARPEYO on eGFR was seen by Month 3 (the earliest assessment) and did not appear to increase in magnitude over two years. At Year 2, there was a 5.9 mL/min/1.73 m2 difference in the mean change from baseline in eGFR between TARPEYO and placebo (95% CI: 3.3 to 8.5 mL/min/1.73 m2; p<0.0001).

Figure 2: LS Mean (95% CI) Change from Baseline in eGFR (mL/min/1.73 m 2) in NefIgArd Study (Full Analysis Set)

Estimated least squares mean change from baseline in eGFR (mL/min/1.73 m2) with 95% confidence intervals estimated from a mixed model repeated measures analysis of post-baseline to baseline differences at 3, 6, 9, 12, 18, and 24 months. Analysis was based on untransformed data and includes all eGFR data regardless of use of prohibited medication at any point during the study. A total of 15 patients in the TARPEYO arm and 20 patients in the placebo arm received rescue medication during the 2-year study.

Abbreviations: eGFR, estimated glomerular filtration rate; CI, confidence interval; LS least squares

The treatment effect based on the change from baseline in eGFR at 2 years was consistent across key subgroups, including key demographic (such as age, sex, race) and baseline disease (such as baseline proteinuria) characteristics.

16 HOW SUPPLIED/STORAGE AND HANDLING

TARPEYO (budesonide) delayed release capsules 4 mg, are white opaque- coated capsules marked with “CAL10 4 MG” in black ink on the body of the capsule. They are supplied as follows:

NDC 81749-004-01: Bottles of 120 capsules. Child-resistant cap.

Store at 20-25°C (68 - 77°F); excursions permitted to 15° to 30°C (59° to 86°F). [See USP Controlled Room Temperature].

Keep container tightly closed. Protect from moisture.

17 PATIENT COUNSELING INFORMATION

Advise the patient to read the FDA-approved patient labeling (Patient Information).

Advise patients that TARPEYO may cause hypercorticism and adrenal axis suppression and to follow a taper schedule, as instructed by their healthcare provider if discontinuing therapy [see Warnings and Precautions (5.1)].

TARPEYO causes immunosuppression. Advise patients to avoid exposure to people with chicken pox or measles and, if exposed, to consult their healthcare provider immediately. There is an increased risk of developing a variety of infections, including worsening of existing tuberculosis, fungal, bacterial, viral or parasitic infections, or ocular herpes simplex, and to contact their healthcare provider if they develop any symptoms of infection [see Warnings and Precautions (5.3)] . Provide advice regarding vaccination schedules for immunocompromised patients.

Advise patients that TARPEYO delayed release capsules should be swallowed whole and not chewed, crushed or broken and to take TARPEYO in the morning, at least 1 hour before a meal [See Dosage and Administration (2)].

Advise patients to avoid the consumption of grapefruit juice for the duration of their TARPEYO therapy [See Drug Interactions (7.1)].

TARPEYO is a registered trademark of Calliditas Therapeutics AB, or its affiliates.

© 2024 Calliditas Therapeutics AB (publ)

Manufactured for and distributed by:
Calliditas Therapeutics AB

Stockholm, Sweden

Patent: http://www.calliditas.com/patents

Patient Information
TARPEYO (tar-PAY-oh)
(budesonide)
delayed release capsules

What is TARPEYO?
TARPEYO is a prescription medicine used to reduce the loss of kidney function in adults with a kidney disease called primary immunoglobulin A nephropathy (IgAN), who are at risk for their disease getting worse.
It is not known if TARPEYO is safe and effective in children.

Do not take TARPEYO ifyou are allergic to budesonide or any of the ingredients in TARPEYO. See the end of this leaflet for a complete list of ingredients in TARPEYO.

Before taking TARPEYO, tell your healthcare provider about all of your medical conditions, including if you:

- have liver problems.
- plan to have surgery.
- have chickenpox or measles or have recently been near anyone with chickenpox or measles.
- have an infection.
- have high blood sugar levels (prediabetes or diabetes).
- have glaucoma or cataracts.
- have a family history of diabetes or glaucoma.
- have or have had tuberculosis.
- have high blood pressure (hypertension).
- have decreased bone mineral density (osteoporosis).
- have stomach ulcers.
- are pregnant or plan to become pregnant. TARPEYO may harm your unborn baby. Talk to your healthcare provider about the possible risk to your unborn baby if you take TARPEYO when you are pregnant.
- are breastfeeding or plan to breastfeed. It is not known if TARPEYO passes into your breast milk or if it will affect your baby. Talk to your healthcare provider about the best way to feed your baby during treatment with TARPEYO.

Tell your healthcare provider about all the medicines you take,including prescription and over-the-counter medicines, vitamins, and herbal supplements. TARPEYO and other medicines may affect each other causing side effects.

How should I take TARPEYO?

- Take TARPEYO exactly as your healthcare provider tells you.
- Your healthcare provider will decide how long you should take TARPEYO. Do not stop taking TARPEYO without first talking with your healthcare provider.
- Take your prescribed dose of TARPEYO 1 time each day in the morning, at least 1 hour before a meal.
- Swallow TARPEYO capsules whole. Do notopen, chew, crush, or break TARPEYO capsules before swallowing.
- If you miss a dose of TARPEYO, take your prescribed dose at your next scheduled time. Do nottake two doses of TARPEYO at the same time.
- If you take too much TARPEYO, call your healthcare provider right away or go to the nearest hospital emergency room.

What should I avoid while taking TARPEYO?
Do noteat grapefruit or drink grapefruit juice during your treatment with TARPEYO. Eating grapefruit or drinking grapefruit juice can increase the level of TARPEYO in your blood.

What are the possible side effects of TARPEYO?
TARPEYO may cause serious side effects, including:

- Effects of having too much corticosteroid medicine in your blood (hypercorticism).Long-time use of TARPEYO can cause you to have signs and symptoms of too much cortisol, a stress hormone in your blood. Tell your healthcare provider if you have any of the following signs and symptoms of hypercorticism:

- acne
- bruise easily
- rounding of your face (moon face)
- ankle swelling

- thicker or more hair on your body and face
- a fatty pad or hump between your shoulders (buffalo hump)
- pink or purple stretch marks on the skin of your abdomen, thighs, breasts, or arms

- Adrenal suppression.When TARPEYO is taken for a long period of time (chronic use), adrenal suppression can happen. This is a condition in which the adrenal glands do not make enough steroid hormones. Symptoms of adrenal suppression include:

- tiredness
- weakness

- nausea and vomiting
- low blood pressure

Tell your healthcare provider if you are under stress or have any symptoms of adrenal suppression during treatment with TARPEYO.

- Risk of immunosuppression.TARPEYO weakens your immune system. Taking medicines that weaken your immune system makes you more likely to get infections. Avoid contact with people who have contagious diseases, such as chickenpox or measles, during treatment with TARPEYO. Tell your healthcare provider right away if you come in contact with anyone who has chickenpox or measles. Consult with your healthcare provider regarding appropriate vaccination scheduling.
- Tell your healthcare provider if you develop any symptoms of infection during treatment with TARPEYO, including:

- fever
- feeling tired
- chills

- aches
- pain
- nausea and vomiting

The most common side effects of TARPEYO include:

- swelling of the lower legs, ankles, and feet
- high blood pressure
- muscle spasms
- acne
- headache
- upper respiratory tract infection

- swelling of the face
- weight increase
- indigestion
- irritation or inflammation of the skin
- joint pain
- increased white blood cell count

These are not all the possible side effects of TARPEYO.
Call your doctor for medical advice about side effects. You may report side effects to FDA at 1-800-FDA-1088.

How should I store TARPEYO?

- Store TARPEYO at room temperature between 68°F to 77°F (20°C to 25°C).
- Keep TARPEYO in a tightly closed container.
- Protect from moisture.

Keep TARPEYO and all medicines out of the reach of children.

General information about the safe and effective use of TARPEYO.
Medicines are sometimes prescribed for purposes other than those listed in a Patient Information leaflet. Do not use TARPEYO for a condition for which it was not prescribed. Do not give TARPEYO to other people, even if they have the same symptoms you have. It may harm them. You can ask your pharmacist or healthcare provider for information about TARPEYO that is written for health professionals.

What are the ingredients in TARPEYO?
Active ingredient:budesonide
Inactive ingredients:sugar spheres (sucrose and starch), hypromellose, polyethylene glycol, citric acid monohydrate, ethyl cellulose, medium chain triglycerides and oleic acid.
The capsules contain: hypromellose and titanium oxide (E171).
The printing ink on the capsules contain: shellac, propylene glycol and black iron oxide (E172).
The enteric coating on the capsules contain: methacrylic acid and methacrylate copolymer, talc and dibutyl sebacate.

Manufactured for and distributed by: Calliditas Therapeutics AB, Stockholm, Sweden
TARPEYO is a trademark of Calliditas Therapeutics AB, or its affiliates.
© 2021 Calliditas Therapeutics AB (publ)
Patent: http://www.calliditas.com/patents
For more information, go to www.TARPEYOTouchpoints.com or call 1-933-444-8277.

This Patient Information has been approved by the U.S. Food and Drug Administration.

Revised: 12/2023

Principal Display Panel - 4 mg Bottle Label

NDC 81749-004-01

TARPEYO™

(budesonide) delayed release capsules

4 mg

120 Capsules

Rx only

Calliditas Therapeutics AB